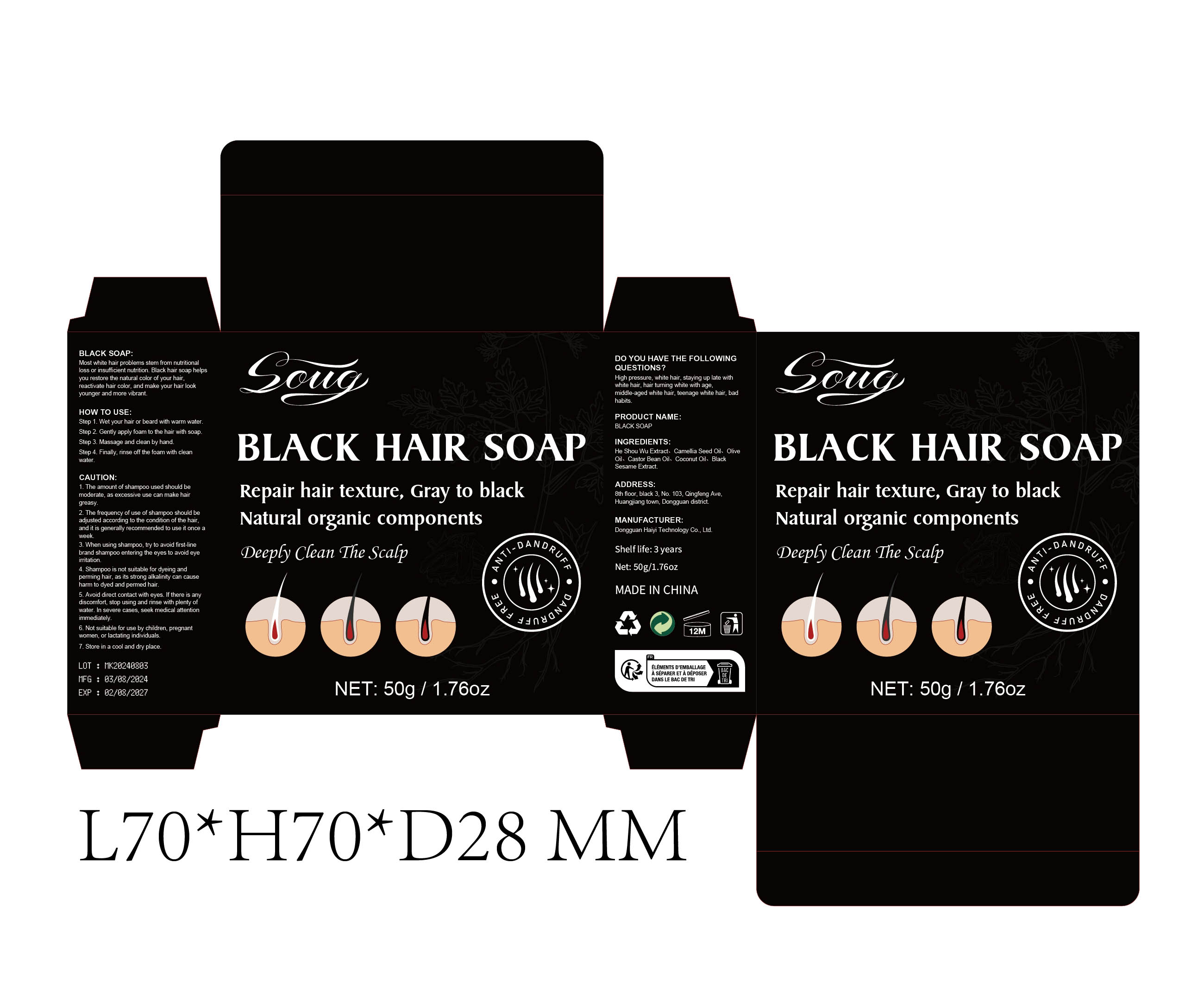 DRUG LABEL: Black Bar
NDC: 84732-007 | Form: SOAP
Manufacturer: Dongguan Haiyi Technology Co.,Ltd.
Category: otc | Type: HUMAN OTC DRUG LABEL
Date: 20240923

ACTIVE INGREDIENTS: POLYGONUM CUSPIDATUM ROOT 1 g/50 g
INACTIVE INGREDIENTS: COCONUT OIL; CAMELLIA KISSII SEED OIL; HYDROGENATED OLIVE OIL; SESAME OIL

Active ingredient

He Shou Wu Extract

Inactive ingredient

Camellia Seed Oil、 OliveOil、Castor Bean Oil、Coconut Oil、Black Sesame Extract.

Purpose section

Repair hair texture, Gray to black Natural organic components

Warning

1. The amount of shampoo used should bemoderate,as excessive use can make hairgreasy
2. The frequency of use of shampoo should beadjusted according to the condition of the hair,and it is generally recommended to use it once aweek.
3. When using shampoo, try to avoid first-linebrand shampoo entering the eyes to avoid eyeirritation.
4. Shampoo is not suitable for dyeing andperming hair, as its strong alkalinity can causeharm to dyed and permed hair.
5. Avoid direct contact with eyes. lf there is anydiscomfort. stop using and rinse with plenty ofwater.In severe cases, seek medical attentonimmediately.
6. Not suitable for use by children, pregnantwomen,or lactating individuals
7. Store in a cool and dry place.

stop use

Shampoo is not suitable for dyeing andperming hair, as its strong alkalinity can causeharm to dyed and permed hair

not use

Not suitable for use by children, pregnantwomen,or lactating individuals.

OUT OF CHILDREN

KEEP THE PRODUCT OUT OF REACH OF CHILDREN to

HOW TO USE

Step 1. Wet your hair or beard with warm water

Step 2. Gently apply foam to the hair with soap

Step 3. Massage and clean by hand

Step 4. Finally, rinse off the foam with cleanwater.

Dosage

2. The frequency of use of shampoo should beadjusted according to the condition of the hair,and it is generally recommended to use it once aweek.